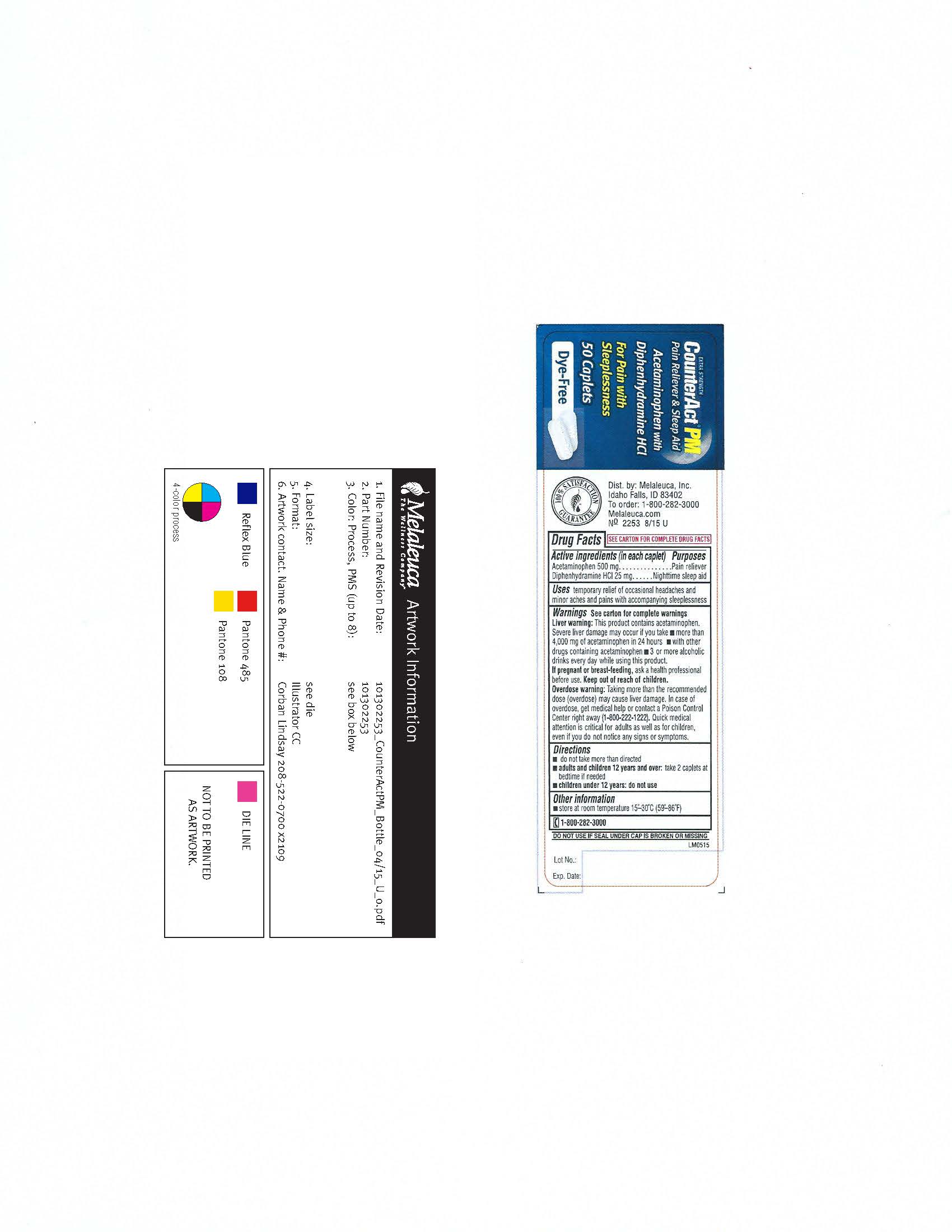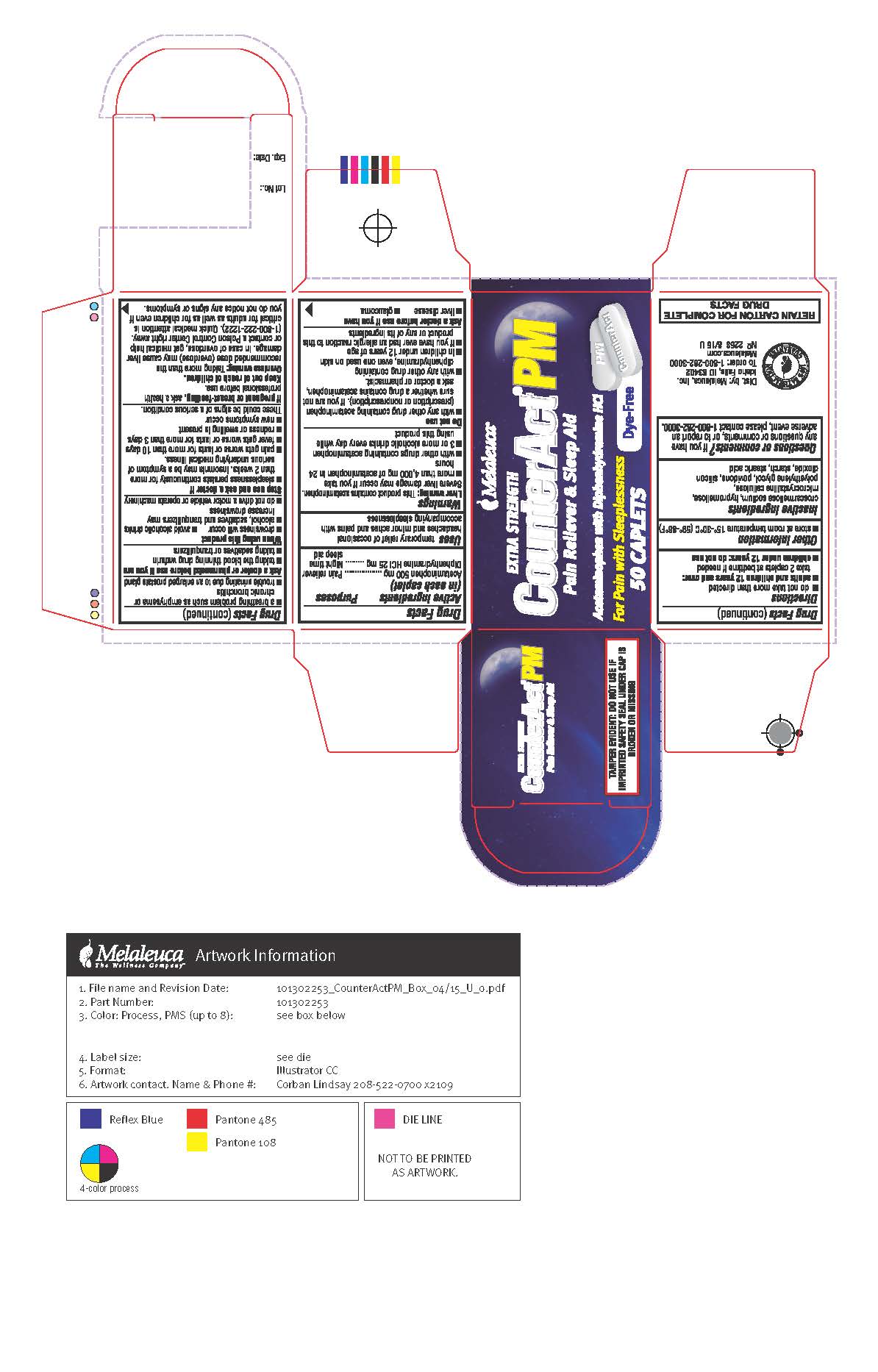 DRUG LABEL: CounterAct
NDC: 54473-304 | Form: TABLET
Manufacturer: Melaleuca, Inc.
Category: otc | Type: HUMAN OTC DRUG LABEL
Date: 20190118

ACTIVE INGREDIENTS: DIPHENHYDRAMINE HYDROCHLORIDE 25 mg/1 1; ACETAMINOPHEN 500 mg/1 1
INACTIVE INGREDIENTS: MICROCRYSTALLINE CELLULOSE; SODIUM STARCH GLYCOLATE TYPE A POTATO; HYPROMELLOSE, UNSPECIFIED; SILICON DIOXIDE; STEARIC ACID; ANHYDROUS CITRIC ACID; PYRROLIDONE; SODIUM CARBONATE; MAGNESIUM STEARATE; MAGNESIUM SILICATE; MALTODEXTRIN; CALCIUM CARBONATE; CROSCARMELLOSE SODIUM; ANHYDROUS LACTOSE; MEDIUM-CHAIN TRIGLYCERIDES; STARCH, CORN

CounterAct PM Content of Label

Active ingredients

Acetaminophen 500 mg

Diphenhydramine HCl 25 mg

Do Not Use

- with any other drug containing acetaminophen (prescription or nonprescription). If you are not sure whether a drug contains acetaminophen, ask a doctor or pharmacist.
- with any other product containing diphenhydramine, even one used on skin
- in children under 12 years of age
- if you are allergic to acetaminophen or any of the ingredients in this product

Warnings

Liver Warning: This product contains acetaminophen. Severe liver damage may occur if you take:

- more than 4,000 mg of acetaminophen in 24 hours, which is the maimum daily amount
- with other drugs containing acetaminophen
- 3 or more alcoholic drinks every day while using this product

Ask a doctor or pharmacist before use if you are

- taking the blood thinning drug warfarin
- taking sedatives or tranquilizers

When using this product

- drowsiness will occur
- avoid alcoholic beverages
- do not drive a motor vehicle or operate machinery

Stop use and ask a doctor if

- sleeplessness persists continuously for more than 2 weeks. Insomnia may be a symptom of a searious underlying medical illness.
- new symptoms occur
- redness or swelling is present
- pain gets worse of lasts more than 10 days
- fever gets worse or lasts more than 3 days

These could be signs of a serious condition

WARNINGS

If pregnant or breast-feeding, ask a health professional before use.

Keep out of reach of children.

Overdose warning: Taking more than the recommended dose (overdose) may cause liver damage. In case of overdose, get medical help or contact a Poison Control Center right away (1-800-222-1222). Quick medical attention is critical for adults as well as for children, even if you do not notice any signs or symptoms.

Keep out of reach of children

Purpose

Pain reliever

Nighttime sleep-aid

Directions

do not take more than directed (see overdose warning)
adults and children 12 years and over: take 2 caplets at bedtime. Do not take more than 2 caplets of this product in 24 hours.
children under 12 years: do not use.

Other Information

- store at controlled room temperature 15-30oC (59-86oF)
- see end flap for expiration date and lot number

Questions or comments?

If you have any questions or comments, or to report an adverse even, please contact 1-800-282-3000.

Inactive ingredients

calcium carbonate, corn starch, citric acid, croscarmellose sodium, hypromellose, lactose, magnesium silicate,

magnesium stearate, maltodextrin, microcrystalline cellulose, medium-chain triglyceride, polyvinylpyrrolidone, pregelatinized starch, silicon dioxide, sodium carbonate, sodium starch glycolate, stearic acid.

Do not take this product unless directed by a doctor if you have

- glaucoma
- trouble urinating due to an enlarged prostate gland
- liver disease
- a breathing problem such as emphysema or chronic bronchitis

Uses

temporary relief of occassional headaches, minor aches, and pains with accompanying sleeplessness